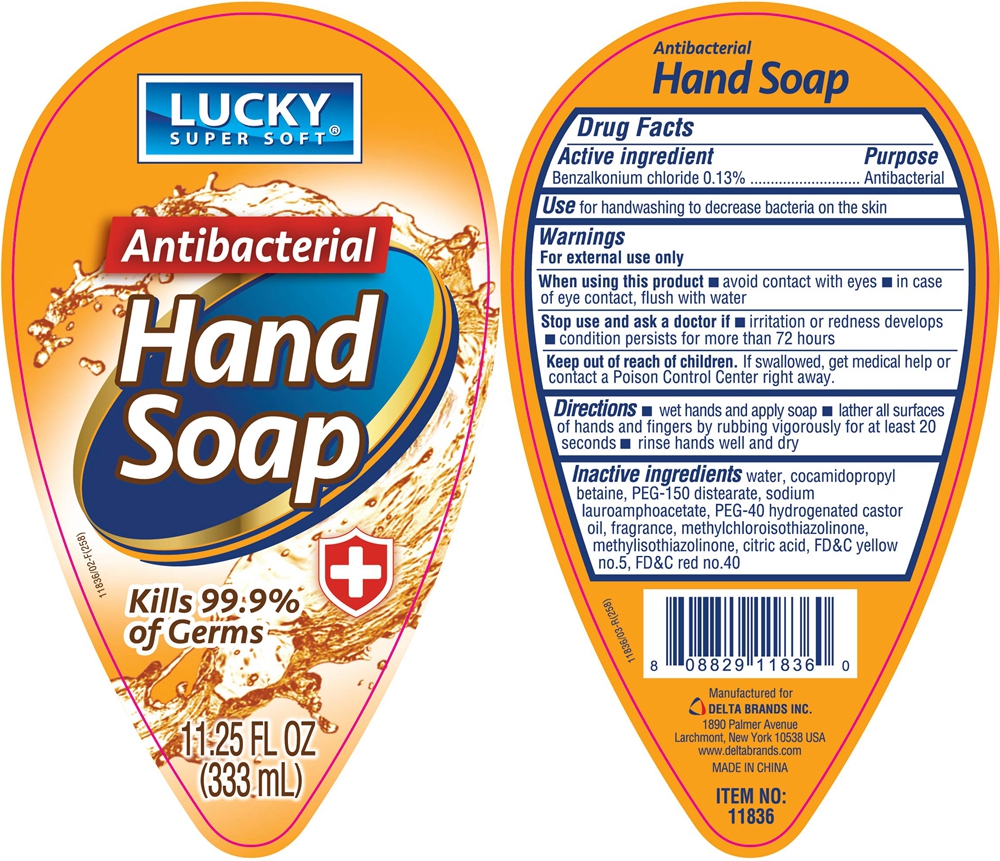 DRUG LABEL: LUCKY SUPER SOFT ANTIBACTERIAL HAND
NDC: 76176-024 | Form: LIQUID
Manufacturer: NINGBO LIYUAN DAILY CHEMICAL PRODUCTS CO., LTD.
Category: otc | Type: HUMAN OTC DRUG LABEL
Date: 20240101

ACTIVE INGREDIENTS: BENZALKONIUM CHLORIDE 0.13 g/100 mL
INACTIVE INGREDIENTS: WATER; COCAMIDOPROPYL BETAINE; SODIUM LAUROAMPHOACETATE; METHYLCHLOROISOTHIAZOLINONE; CITRIC ACID MONOHYDRATE; METHYLISOTHIAZOLINONE; FD&C YELLOW NO. 5; PEG-150 DISTEARATE; HYDROGENATED CASTOR OIL; FD&C RED NO. 40

Active ingredient

Benzalkonium chloride 0.13 percent

Purpose

Antibacterial

Use

for handwahing to decrease bacteria on the skin

Warnings

For external use only.

When using this product

avoid contact with eyes, in case of eye contact, flush with water.

Stop use and ask a doctor if

irritation or redness develops, condition persists for more than 72 hours.

Keep out of reach of children.

If swallowed, get medical help or contact a Poison Control Center right away.

Directions

wet hands and apply soap.

lather all surfaces of hands and fingers by rubbing vigorously for at leat 20 seconds.

rinse hands well and dry.

Inactive ingredients

water, cocamidopropyl betaine, PEG-150 distearate, sodium lauroamphoacetate, PEG-40 hydrogenated castor oil, fragrance, methylchloroisothiazolinone, methylisothiazolinone, citric acid, FD&C yellow no.5, FD&C red no.40